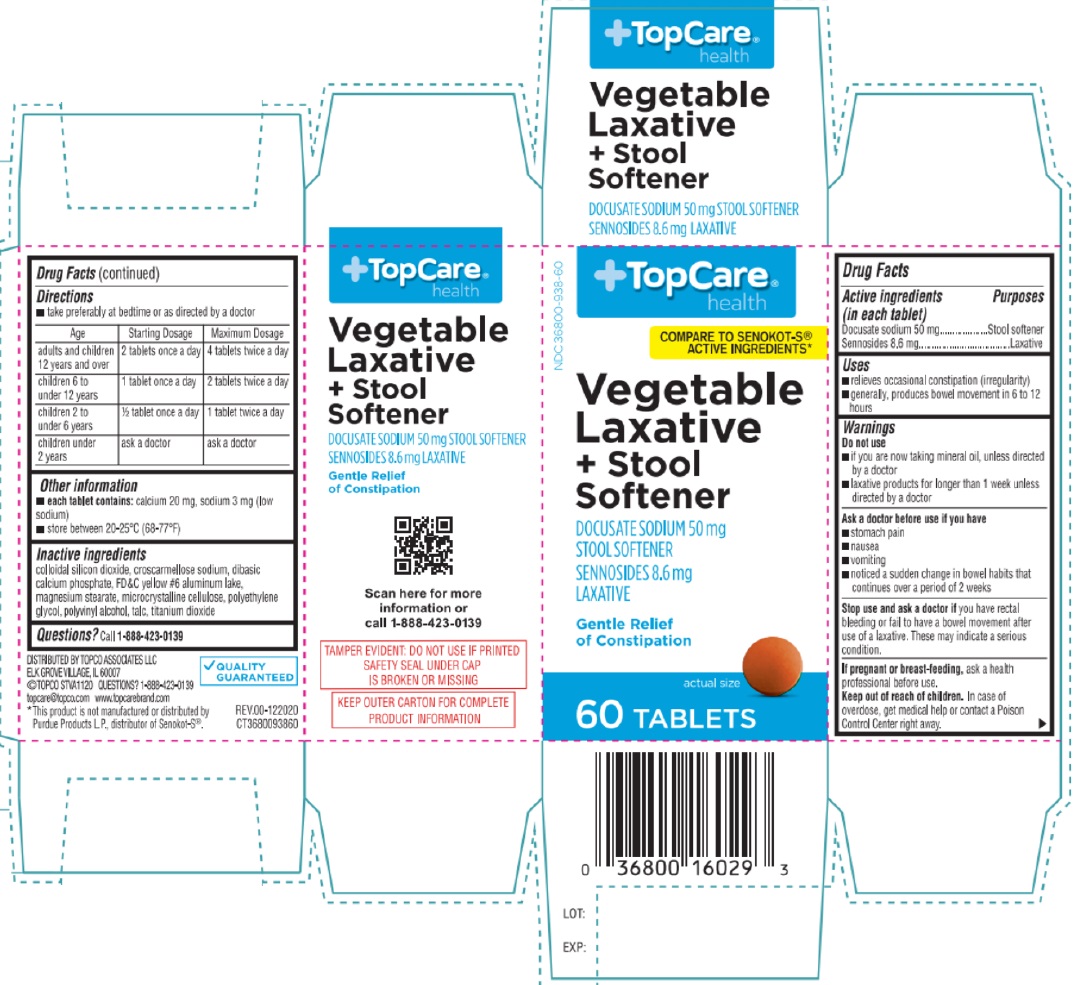 DRUG LABEL: Vegetable Laxative and Stool Softner
NDC: 36800-938 | Form: TABLET, COATED
Manufacturer: TOPCO ASSOCIATES LLC
Category: otc | Type: HUMAN OTC DRUG LABEL
Date: 20250101

ACTIVE INGREDIENTS: DOCUSATE SODIUM 50 mg/1 1; SENNOSIDES 8.6 mg/1 1
INACTIVE INGREDIENTS: SILICON DIOXIDE; CROSCARMELLOSE SODIUM; ANHYDROUS DIBASIC CALCIUM PHOSPHATE; FD&C YELLOW NO. 6 ALUMINUM LAKE; MAGNESIUM STEARATE; MICROCRYSTALLINE CELLULOSE; POLYETHYLENE GLYCOL, UNSPECIFIED; POLYVINYL ALCOHOL, UNSPECIFIED; TALC; TITANIUM DIOXIDE

Vegetable Laxative and Stool Softner

Active ingredients (in each tablet)

Docusate sodium 50 mg
Sennosides 8.6 mg

Purposes

Stool softener
Laxative

Uses

• relieves occasional constipation (irregularity)
• generally, produces bowel movement in 6 to 12 hours

Warnings

Do not use
• if you are now taking mineral oil, unless directed by a doctor
• laxative products for longer than 1 week unless directed by a doctor

Ask a doctor before use if you have
• stomach pain
• nausea
• vomiting
• noticed a sudden change in bowel habits that continues over a period of 2 weeks

Stop use and ask a doctor if you have rectal bleeding or fail to have a bowel movement after use of a laxative. These may indicate a serious condition.

If pregnant or breast-feeding, ask a health professional before use.

Keep out of reach of children. In case of overdose, get medical help or contact a Poison Control Center right away.

Directions

• take preferably at bedtime or as directed by a doctor

Age | Starting Dosage | Maximum Dosage
adults and children 12 years and over | 2 tablets once a day | 4 tablets twice a day
children 6 to under 12 years | 1 tablet once a day | 2 tablets twice a day
children 2 to under 6 years | ½ tablet once a day | 1 tablet twice a day
children under 2 years | ask a doctor | ask a doctor

Other information

• each tablet contains: calcium 20 mg, sodium 3 mg (low sodium)
• store between 20-25°C (68-77°F)

Inactive ingredients

colloidal silicon dioxide, croscarmellose sodium, dibasic calcium phosphate, FD&C yellow #6 aluminum lake, magnesium stearate, microcrystalline cellulose, polyethylene glycol, polyvinyl alcohol, talc, titanium dioxide

Questions?

Call 1-888-423-0139

+TopCare®
health

COMPARE TO SENOKOT-S® ACTIVE INGREDIENTS*

Vegetable Laxative + Stool Softener

Gentle Relief of Constipation

TAMPER EVIDENT: DO NOT USE IF PRINTED SAFETY SEAL UNDER CAP IS BROKEN OR MISSING

KEEP OUTER CARTON FOR COMPLETE PRODUCT INFORMATION

DISTRIBUTED BY TOPCO ASSOCIATES LLC
ELK GROVE VILLAGE, IL 60007
©TOPCO STVA1120
topcare@topco.com www.topcarebrand.com

*This product is not manufactured or distributed by Purdue Products L.P., distributor of Senokot-S®.